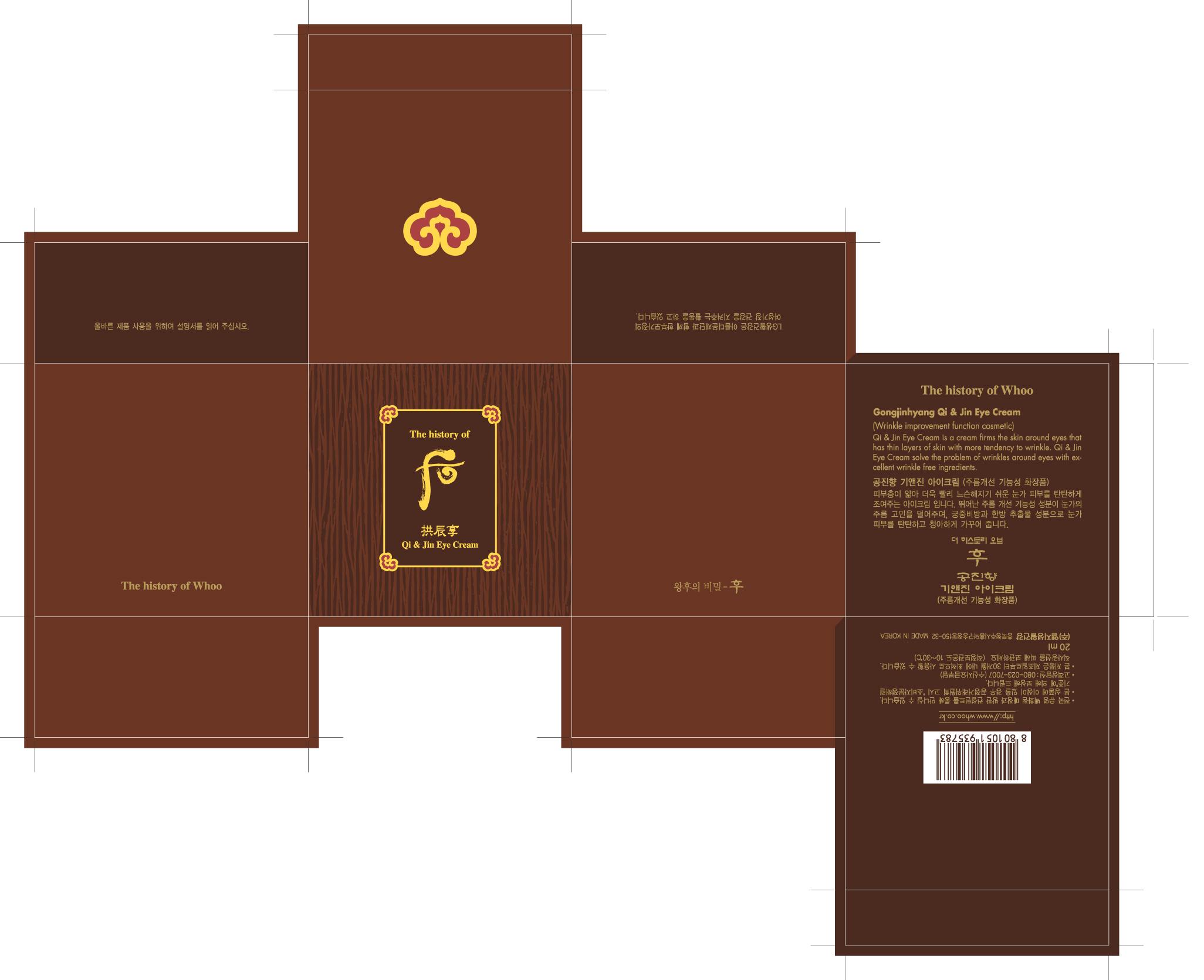 DRUG LABEL: Gongjinhyang Qi and Jin Eye
NDC: 53208-500 | Form: CREAM
Manufacturer: LG Household and Healthcare, Inc.
Category: otc | Type: HUMAN OTC DRUG LABEL
Date: 20110222

ACTIVE INGREDIENTS: .GAMMA.-AMINOBUTYRIC ACID 0.022 mL/100 mL
INACTIVE INGREDIENTS: WATER; PANTHENOL; CYCLOMETHICONE 5; GLYCERIN; METHYLPARABEN; GLYCERYL MONOSTEARATE; ETHYLPARABEN; MACADAMIA OIL; MEDIUM-CHAIN TRIGLYCERIDES; DIPROPYLENE GLYCOL; EDETATE TRISODIUM; AQUILARIA MALACCENSIS STEM; POLYETHYLENE GLYCOL 3350; FD&C YELLOW NO. 6; FD&C YELLOW NO. 5

Drug Facts

ACTIVE INGREDIENT

.GAMMA.-AMINOBUTYRIC ACID 0.022mL/100mL

WARNINGS AND PRECAUTIONS

For external use only.

Keep out of reach of children. Is swallowed, get medical help or contact a Poison Control Center right away.

WHEN USING

Keep out of eyes. Rinse with water to remove.

STOP USE

Stop use if a rash or irritation develops and lasts.

PACKAGE LABEL

The History of Whoo
Qi and Jin Eye Cream

PURPOSE

Anti-Wrinkle

INDICATIONS AND USAGE

Apply after the essence.

DOSAGE AND ADMINISTRATION

Apply in the morning and evening after essence. Pump 1 time in your fingertip and gently massage the eye area.

INACTIVE INGREDIENT

WATER, DIPROPYLENE GLYCOL, CYCLOMETHICONE 5, GLYCERIN, GLYCERYL STEARATE, MACADAMIA OIL, MEDIUM-CHAIN TRIGLYCERIDES, PANTHENOL, AQUILARIA MALACCENSIS STEM, METHYLPARABEN, ETHYLPARABEN, POLYETHYLENE GLYCOL 3350, EDETATE TRISODIUM, FD C YELLOW NO. 5F, D C YELLOW NO. 6.